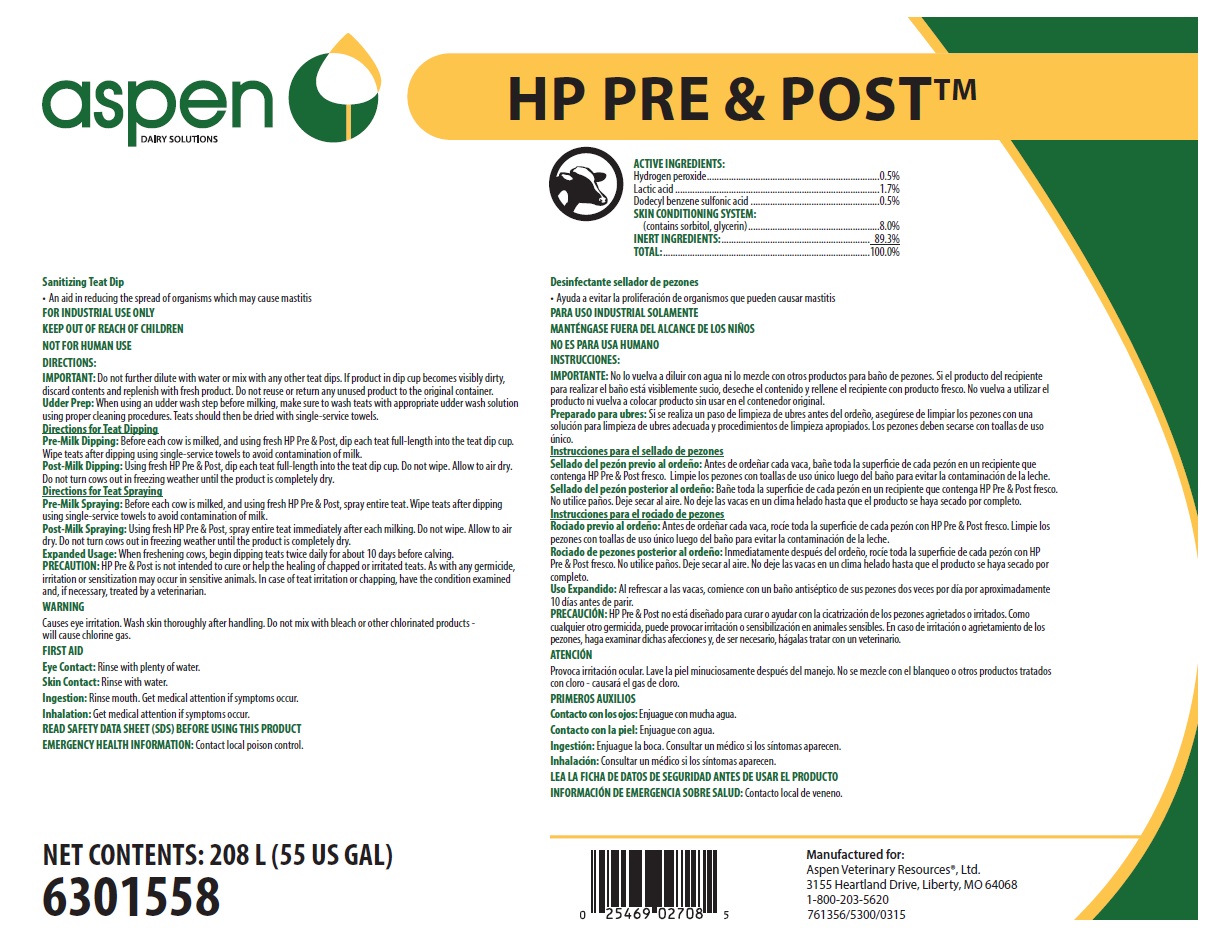 DRUG LABEL: HP Pre and Post
NDC: 46066-404 | Form: SOLUTION
Manufacturer: Animal Health International, Inc.
Category: animal | Type: OTC ANIMAL DRUG LABEL
Date: 20250626

ACTIVE INGREDIENTS: HYDROGEN PEROXIDE 5 mg/1 mL; LACTIC ACID 17 mg/1 mL; DODECYLBENZENESULFONIC ACID 5 mg/1 mL
INACTIVE INGREDIENTS: SORBITOL; GLYCERIN; WATER

SAFE HANDLING WARNING

FOR INDUSTRIAL USE ONLY

KEEP OUT OF REACH OF CHILDREN

NOT FOR HUMAN USE

WARNING

Causes eye irritation. Wash skin thoroughly after handling. Do not mix with bleach or other chlorinated products - will cause chlorine gas

DIRECTIONS:

IMPORTANT: Do not further dilute with water or mix with any other teat dips. If product in dip cup becomes visibly dirty, discard contents and replenish with fresh product. Do not reuse or return any unused product to the original container. Udder Prep: When using an udder wash step before milking, make sure to wash teats with appropriate udder wash solution using proper cleaning procedures. Teats should then be dried with single-service towels.

Directions for Teat Dipping

Pre-Milk Dipping: Before each cow is milked, and using fresh HP Pre & Post, dip each teat full-length into the teat dip cup. Wipe teats after dipping using single-service towels to avoid contamination of milk.

Post-Milk Dipping: Using fresh HP Pre & Post, dip each teat full-length into the teat dip cup. Do not wipe. Allow to air dry. Do not turn cows out in freezing weather until the product is completely dry.

Directions for Teat Spraying

Pre-Milk Spraying: Before each cow is milked, and using fresh HP Pre & Post, spray entire teat. Wipe teats after dipping using single-service towels to avoid contamination of milk.

Post-Milk Spraying: Using fresh HP Pre & Post, spray entire teat immediately after each milking. Do not wipe. Allow to air dry. Do not turn cows out in freezing weather until the product is completely dry.

Expanded Usage: When freshening cows, begin dipping teats twice daily for about 10 days before calving. PRECAUTION: HP Pre & Post is not intended to cure or help the healing of chapped or irritated teats. As with any germicide, irritation or sensitization may occur in sensitive animals. In case of teat irritation or chapping, have the condition examined and, if necessary, treated by a veterinarian.

OTHER SAFETY INFORMATION

FIRST AID

Eye Contact: Rinse with plenty of water.

Skin Contact: Rinse with water.

Ingestion: Rinse mouth. Get medical attention if symptoms occur.

Inhalation: Get medical attention if symptoms occur.

READ SAFETY DATA SHEET (SDS) BEFORE USING THIS PRODUCT

EMERGENCY HEALTH INFORMATION: Contact local poison control.

Representative Label and Principal Display

aspen
DAIRY SOLUTIONS

HP PRE & POST™

Sanitizing Teat Dip

- An aid in reducing the spread of organisms which may cause mastitis

ACTIVE INGREDIENTS:
Hydrogen peroxide........................................................................0.5%
Lactic acid.....................................................................................1.7%
Dodecyl benzene sulfonic acid......................................................0.5%
SKIN CONDITIONING SYSTEM:
(contains sorbitol, glycerin).......................................................8.0%
INERT INGREDIENTS:.............................................................. 89.3%
TOTAL:......................................................................................100.0%

Manufactured for:
Aspen Veterinary Resources®, Ltd.
3155 Heartland Drive, Liberty, MO 64068
1-800-203-5620
761356/5300/0315 6301558

NET CONTENTS: 208 L (55 US GAL)

6301558